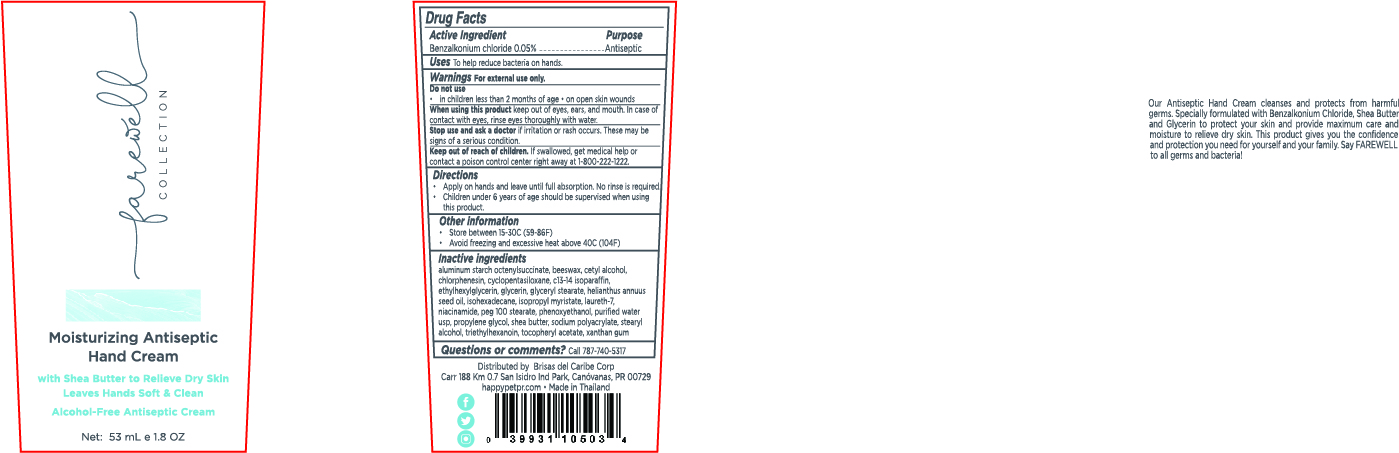 DRUG LABEL: Farewell Collection
NDC: 12961-113 | Form: CREAM
Manufacturer: Brisas del Caribe Corp.	
Category: otc | Type: HUMAN OTC DRUG LABEL
Date: 20210621

ACTIVE INGREDIENTS: BENZALKONIUM CHLORIDE 0.05 mg/100 mL
INACTIVE INGREDIENTS: CYCLOMETHICONE 5; LAURETH-7; CHLORPHENESIN; PHENOXYETHANOL; STEARYL ALCOHOL; NIACINAMIDE; SUNFLOWER OIL; GLYCERIN; WATER; SHEA BUTTER; PEG-100 STEARATE; C13-14 ISOPARAFFIN; YELLOW WAX; ETHYLHEXYLGLYCERIN; CETYL ALCOHOL; ISOPROPYL MYRISTATE; PROPYLENE GLYCOL; ISOHEXADECANE; ALUMINUM STARCH OCTENYLSUCCINATE; GLYCERYL MONOSTEARATE; TRIETHYLHEXANOIN; ALPHA-TOCOPHEROL ACETATE; XANTHAN GUM

Brisas-Paveemol Hand Cream

Active Ingredient(s)

Benzalkonium chloride 0.05 %.

Purpose

Antiseptic

Use

To help reduce bacteria on hands.

Warnings

For external use only.

Do not use

- in children less than 2 months of age
- on open skin wounds

When using this product keep out of eyes, ears, and mouth. In case of contact with eyes, rinse eyes thoroughly with water.
Stop use and ask a doctor if irritation or rash occurs. These may be signs of a serious condition.
Keep out of reach of children. If swallowed, get medical help or contact a Poison Control Center right away.

Stop use and ask a doctor if irritation or rash occurs. These may be signs of a serious condition.

Keep out of reach of children. If swallowed, get medical help or contact a Poison Control Center right away 1 800-222-1222

Directions

- Apply on hands and leave until full absorption. No rinse is required.
- Supervise children under 6 years of age when using this product to avoid swallowing.

Other information

- Store between 15-30C (59-86F)
- Avoid freezing and excessive heat above 40C (104F)

Inactive ingredients

aluminum starch octenylsuccinate, beeswax, cetyl alcohol, chlorphenesin, cyclopentasiloxane, C13-14 isoparaffin, ethylhexylglycerin, glycerin, glyceryl stearate, helianthus annuus seed oil, isohexadecane, isopropyl myristate, laureth-7, niacinamide, PEG 100 stearate, phenoxyethanol, purified water USP, propylene glycol, shea butter, sodium polyacrylate, stearyl alcohol, triethylhexanoin, tocopheryl acetate, xanthan gum

Package Label - Principal Display Panel

53 mL NDC : 12961-113-11